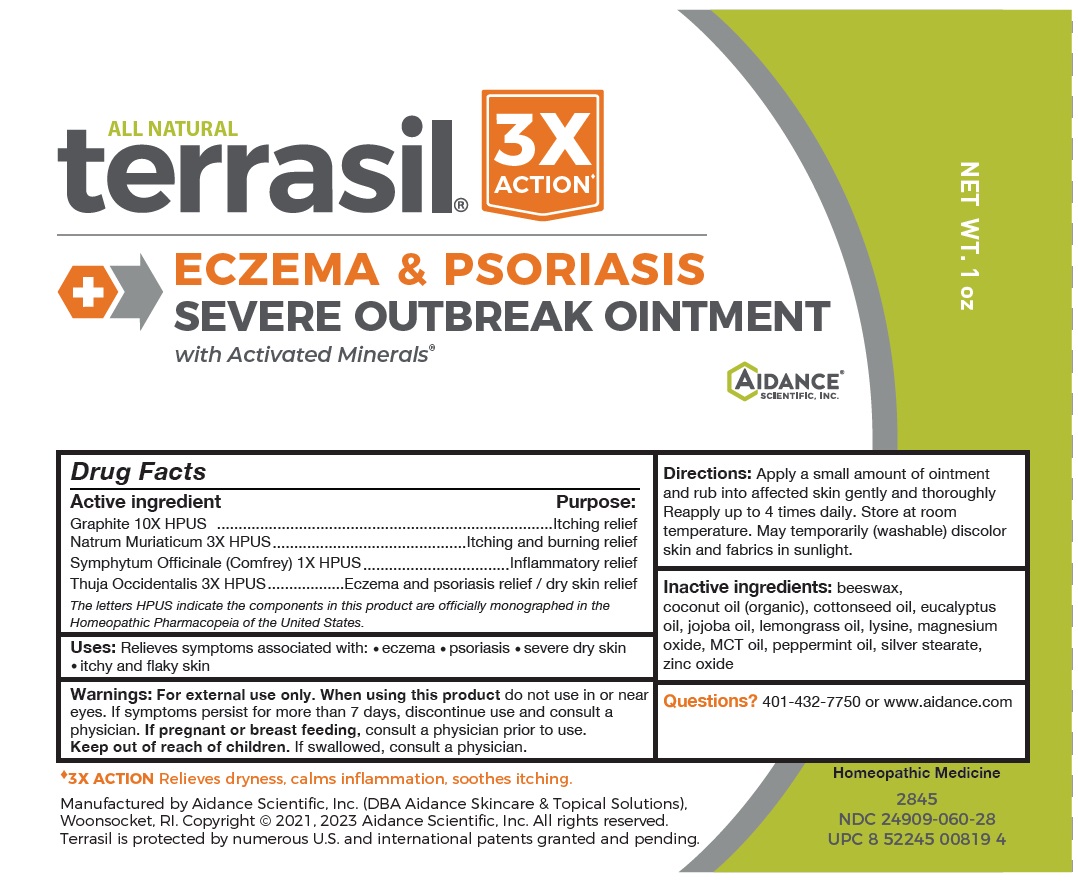 DRUG LABEL: terrasil Eczema and Psoriasis Severe Outbreak
NDC: 24909-060 | Form: OINTMENT
Manufacturer: Aidance Scientific, Inc, DBA Aidance Skincare & Topical Solutions
Category: homeopathic | Type: HUMAN OTC DRUG LABEL
Date: 20231130

ACTIVE INGREDIENTS: GRAPHITE 10 [hp_X]/1 g; SODIUM CHLORIDE 3 [hp_X]/1 g; SYMPHYTUM OFFICINALE WHOLE 1 [hp_X]/1 g; THUJA OCCIDENTALIS LEAFY TWIG 3 [hp_X]/1 g
INACTIVE INGREDIENTS: YELLOW WAX; COCONUT OIL; COTTONSEED OIL; EUCALYPTUS OIL; JOJOBA OIL; WEST INDIAN LEMONGRASS OIL; LYSINE; MAGNESIUM OXIDE; PALM OIL; PEPPERMINT OIL; SILVER STEARATE; ZINC OXIDE

Drug Facts

Active Ingredient Purpose

Graphite 10X HPUS .................................................... Itching relief

Natrum Muriaticum 3X HPUS .................................. Itching & burning relief

Symphytum Officinale (Comfrey) 1X HPUS .............Inflammatory relief

Thuja Occidentalis 3X HPUS..................................... Eczema and psoriasis relief / dry skin relief

The letters HPUS indicate the components in this product are officially monographed in the Homeopathic Pharmacopeia of the United States.

Uses

Relieves symptoms associated with: • eczema • psoriasis • severe dry skin • itchy and flaky skin

Warnings

For external use only. When using this productdo not use in or near eyes. If symptoms persist for more than 7 days, discontinue use and consult a physician. If pregenant or breast feeding, consult a physician prior to use. Keep out of reach of children. If swallowed, consult a physician.

Directions

Apply a small amount of oinment and rub into affected skin gently and thoroughly. Reapply up to 4 times daily.

Store at room temperature. May temporarily (washable) discolor skin and fabrics in sunlight.

Inactive Ingredients

beeswax, coconut oil (organic), cottonseed oil, eucalyptus oil, jojoba oil, lemongrass oil, lysine, magnesium oxide, MCT oil, peppermint oil, silver stearate, zinc oxide